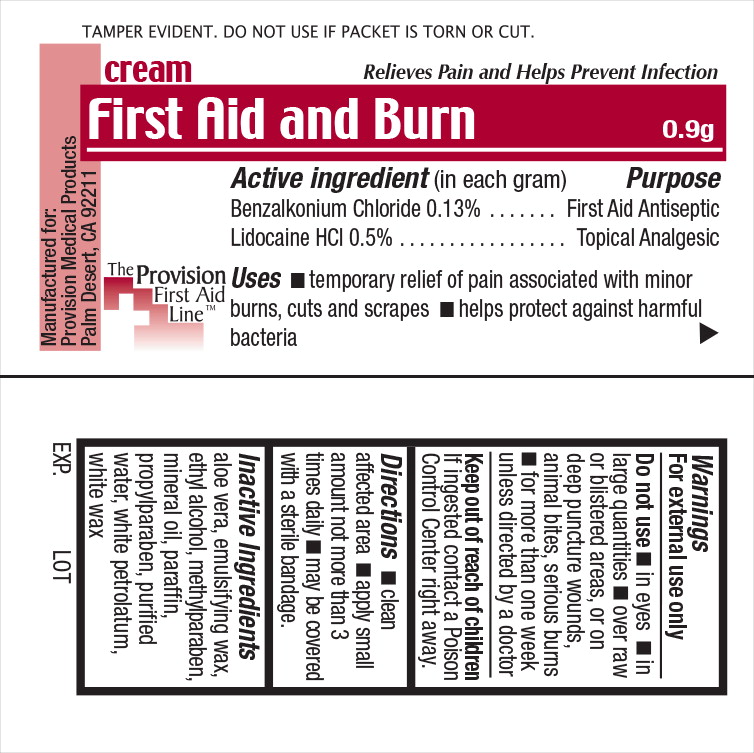 DRUG LABEL: First Aid
NDC: 69103-3553 | Form: CREAM
Manufacturer: Provision Medical
Category: otc | Type: HUMAN OTC DRUG LABEL
Date: 20141202

ACTIVE INGREDIENTS: benzalkonium chloride 1.3 mg/1 g; lidocaine 5.0 mg/1 g
INACTIVE INGREDIENTS: aloe vera leaf; alcohol; methylparaben; mineral oil; paraffin; propylparaben; water; petrolatum; white wax

Active ingredient (in each gram)

Benzalkonium Chloride 0.13%

Lidocaine HCl 0.5%

Purpose

First Aid Antiseptic

Topical Analgesic

Uses

- temporary relief of pain associated with minor burns, cuts and scrapes
- helps protect against harmful bacteria

Warnings

For external use only

Do not use

- in eyes
- in large quantities
- over raw or blistered areas, or on deep puncture wounds, animal bites, serious burns
- for more than one week unless directed by a doctor

Keep out of reach of children If ingested contact a Poison Control Center right away.

Directions

- clean affected area
- apply small amount not more than 3 times daily
- may be covered with a sterile bandage.

Inactive Ingredients

aloe vera, emulsifying wax, ethyl alcohol, methylparaben, mineral oil, paraffin, propylparaben, purified water, white petrolatum, white wax

Manufactured for:
Provision Medical Products
Palm Desert, CA 92211

Principal Display Panel - Pouch Label

TAMPER EVIDENT. DO NOT USE IF PACKET IS TORN OR CUT.

cream Relieves Pain and Helps Prevent Infection

First Aid and Burn 0.9g

The Provision
First Aid
Line™